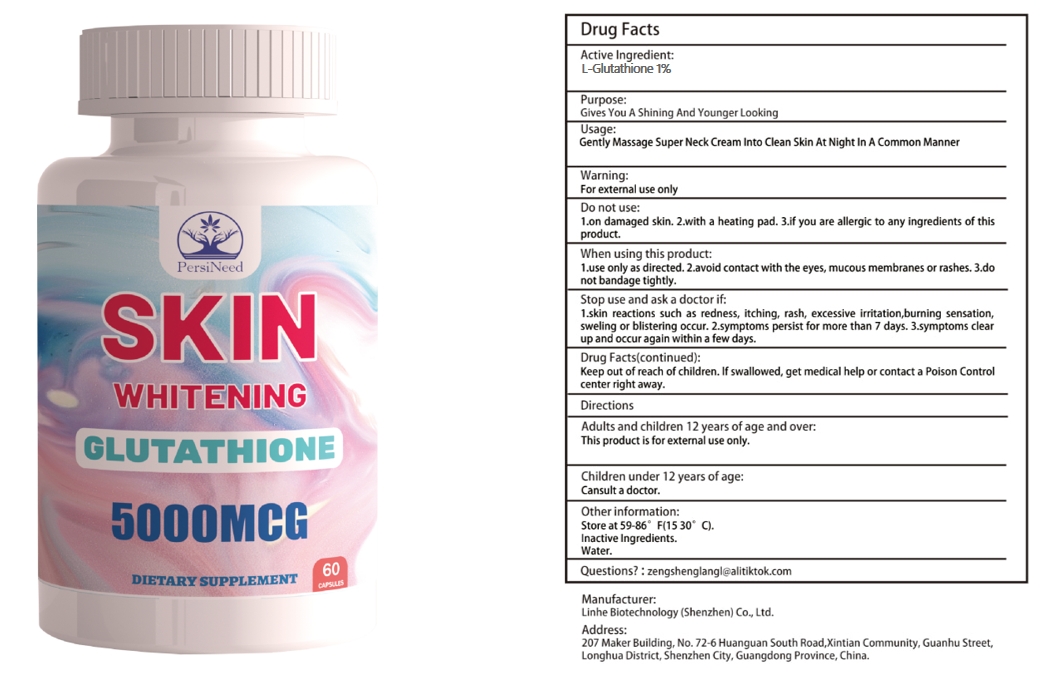 DRUG LABEL: SKIN GLUTATHIONE
NDC: 84575-061 | Form: CAPSULE
Manufacturer: Linhe Biotechnology (Shenzhen) Co., Ltd
Category: otc | Type: HUMAN OTC DRUG LABEL
Date: 20241120

ACTIVE INGREDIENTS: S-(N,N-DIETHYLDITHIOCARBAMOYL)-L-GLUTATHIONE 0.3 g/30 g
INACTIVE INGREDIENTS: CINNAMON

SKIN GLUTATHIONE

ACTIVE INGREDIENT

L-Glutathione 1%

PURPOSE

Dietary Supplement

INDICATIONS AND USAGE

Preferably with a meal and water, or as directed by a health care professional.

WARNINGS

Minors, pregnant women, and breastfeeding mothers are not allowed to consume.This product is notintended to diagnose,treat, cure or prevent any disease.

DOSAGE AND ADMINISTRATION

Contains no wheat, eggs, artificial colours, flavours or preservatives.As a dietary supplement, take 2 capsules once per day.

INACTIVE INGREDIENT

CINNAMON

STORAGE AND HANDLING

Store in a cool and dark place away from light

Keep out of reach of children,in case of overdose, get medical help or contact a PoisonControl Center right away.